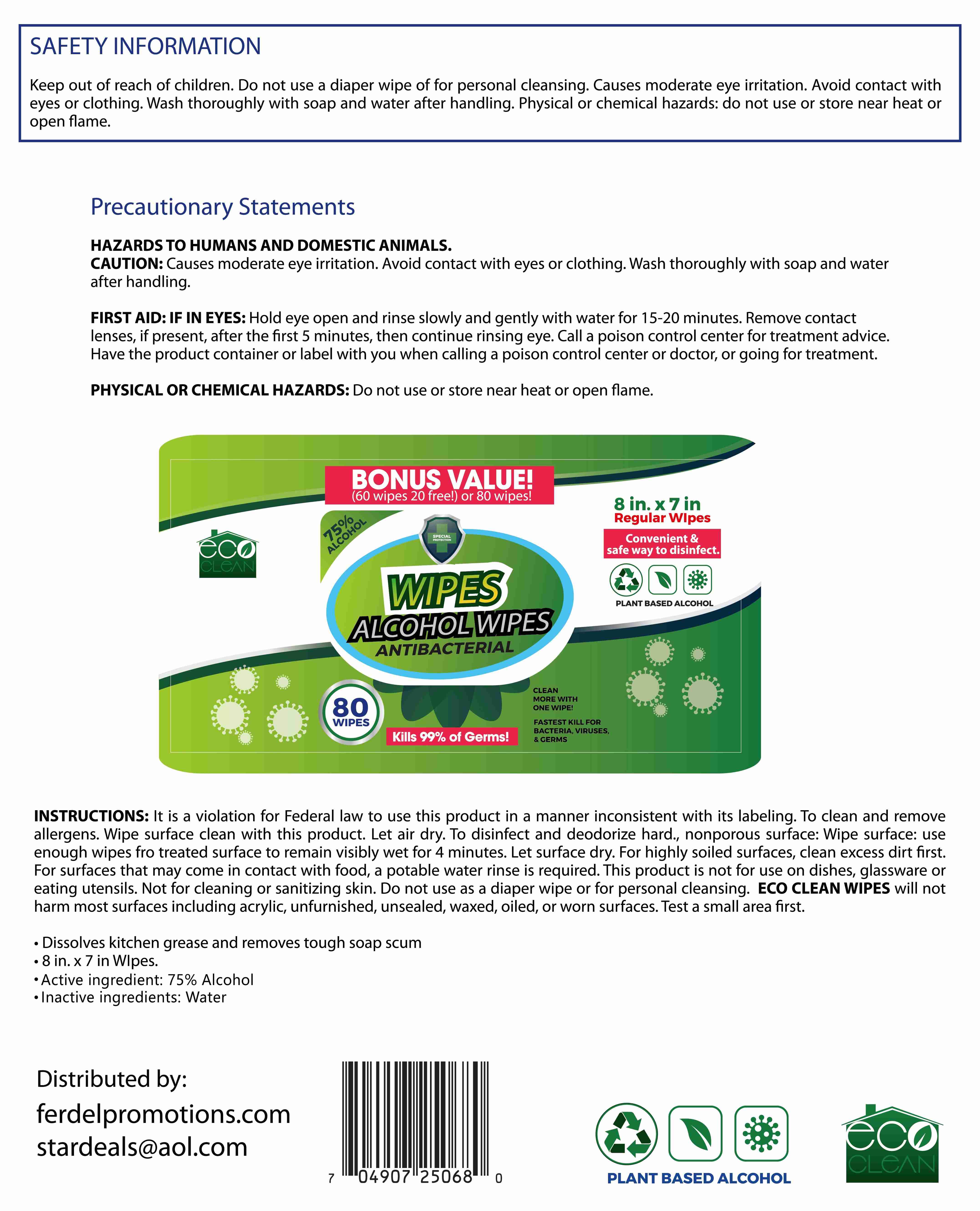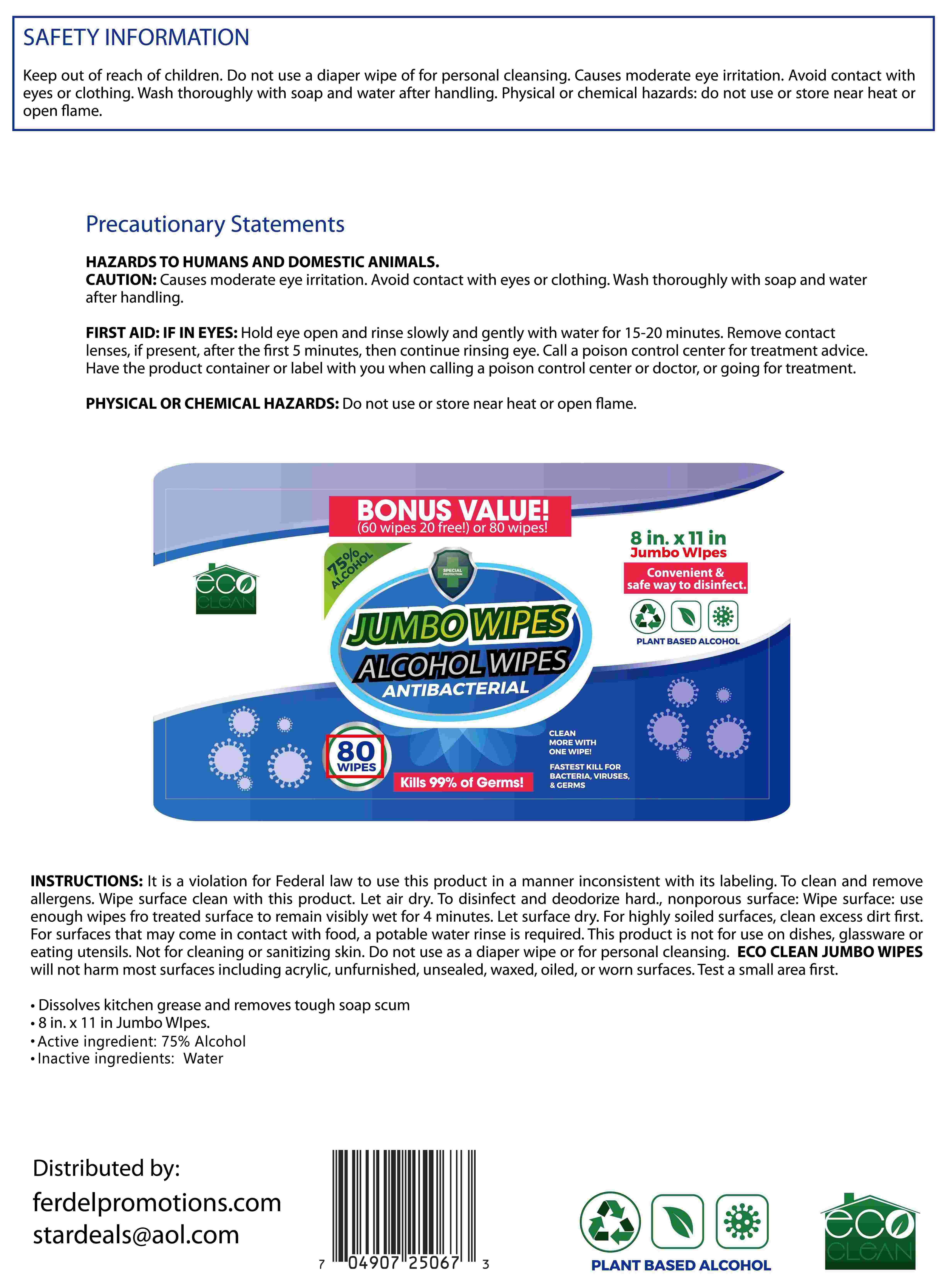 DRUG LABEL: WIPES
NDC: 76991-012 | Form: CLOTH
Manufacturer: Hefei Wenqi Industrial & Trade Co., Ltd
Category: otc | Type: HUMAN OTC DRUG LABEL
Date: 20200910

ACTIVE INGREDIENTS: ALCOHOL 75 mL/100 1
INACTIVE INGREDIENTS: WATER

76991-012
WIPES

Active Ingredient(s)

Alconol 75%

Purpose

Antimicrobial

Use

/

Warnings

CAUTION: Causes moderate eye irritation. Avoid contact with eyes or clothing. Wash thoroughly with soap and water after handling.

FIRST AID: IF IN EYES: Hold eye open and rinse slowly and gently with water for 15-20 minutes. Remove contact lenses, if present, after the first 5 minutes, then continue rinsing eye. Call a poison control center for treatment advice.
Have the product container or label with you when calling a poison control center or doctor, or going for treatment.

PHYSICAL OR CHEMICAL HAZARDS: Do not use or store near heat or open flame.

Do not use

PHYSICAL OR CHEMICAL HAZARDS: Do not use or store near heat or open flame.

WHEN USING

CAUTION: Causes moderate eye irritation. Avoid contact with eyes or clothing. Wash thoroughly with soap and water after handling.

FIRST AID: IF IN EYES: Hold eye open and rinse slowly and gently with water for 15-20 minutes. Remove contact lenses, if present, after the first 5 minutes, then continue rinsing eye. Call a poison control center for treatment advice.
Have the product container or label with you when calling a poison control center or doctor, or going for treatment.

PHYSICAL OR CHEMICAL HAZARDS: Do not use or store near heat or open flame.

STOP USE

/

Keep out of reach of children Do not use a diaper wipe of for personal cleansing

Directions

INSTRUCTIONS: It is a violation for Federal law to use this product in a manner inconsistent with its labeling. To clean and removeal ergens. Wipe surface clean with this product. Let air dry. To disinfect and deodorize hard., nonporous surface: Wipe surface: use enough wipes fro treated surface to remain visibly wet for 4 minutes. Let surface dry. For highly soiled surfaces, clean excess dirt first.
For surfaces that may come in contact with food, a potable water rinse is required. This product is not for use on dishes, glassware or eating utensils. Not for cleaning or sanitizing skin. Do not use as a diaper wipe or for personal cleansing. ECO CLEAN JUMBO WIPES will not harm most surfaces including acrylic, unfurnished, unsealed, waxed, oiled, or worn surfaces. Test a small area first.

Other information

/

Inactive ingredients

water